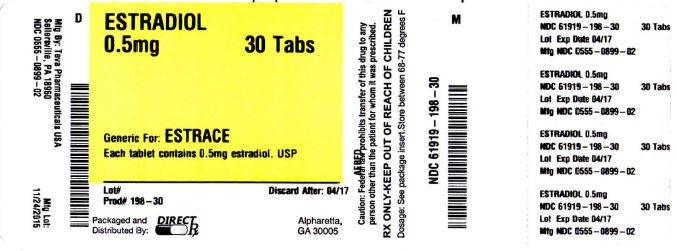 DRUG LABEL: ESTRADIOL
NDC: 61919-198 | Form: TABLET
Manufacturer: DirectRX
Category: prescription | Type: HUMAN PRESCRIPTION DRUG LABEL
Date: 20151125

ACTIVE INGREDIENTS: ESTRADIOL 0.5 mg/1 1
INACTIVE INGREDIENTS: SILICON DIOXIDE; STARCH, CORN; CALCIUM PHOSPHATE, DIBASIC, ANHYDROUS; LACTOSE MONOHYDRATE; MAGNESIUM STEARATE; SODIUM STARCH GLYCOLATE TYPE A POTATO

ESTRADIOL

SPL Unclassified

ESTRADIOLTABLETS USP

Rx only

11001658

Iss. 3/2010

0899

0886

0887

ESTROGENS INCREASE THE RISK OF ENDOMETRIAL CANCER

Close clinical surveillance of all women taking estrogens is important. Adequate diagnostic measures, including endometrial sampling when indicated, should be undertaken to rule out malignancy in all cases of undiagnosed persistent or recurring abnormal vaginal bleeding. There is no evidence that the use of “natural” estrogens results in a different endometrial risk profile than “synthetic” estrogens at equivalent estrogen doses. (See WARNINGS, Malignant neoplasms, Endometrial cancer.)

CARDIOVASCULAR AND OTHER RISKS

Estrogens with or without progestins should not be used for the prevention of cardiovascular disease. (See WARNINGS, Cardiovascular disorders.)

The Women’s Health Initiative (WHI) study reported increased risks of myocardial infarction, stroke, invasive breast cancer, pulmonary emboli, and deep vein thrombosis in postmenopausal women (50 to 79 years of age) during 5 years of treatment with oral conjugated estrogens (CE 0.625 mg) combined with medroxyprogesterone acetate (MPA 2.5 mg) relative to placebo. (See CLINICAL PHARMACOLOGY, Clinical Studies.)

The Women’s Health Initiative Memory Study (WHIMS), a substudy of WHI, reported increased risk of developing probable dementia in postmenopausal women 65 years of age or older during 4 years of treatment with oral conjugated estrogens plus medroxyprogesterone acetate relative to placebo. It is unknown whether this finding applies to younger postmenopausal women or to women taking estrogen alone therapy. (See CLINICAL PHARMACOLOGY, Clinical Studies.)

Other doses of oral conjugated estrogens with medroxyprogesterone acetate, and other combinations and dosage forms of estrogens and progestins were not studied in the WHI clinical trials and, in the absence of comparable data, these risks should be assumed to be similar. Because of these risks, estrogens with or without progestins should be prescribed at the lowest effective doses and for the shortest duration consistent with treatment goals and risks for the individual woman.

Description

Estradiol Tablets USP for oral administration contains 0.5, 1 or 2 mg of micronized estradiol per tablet. Estradiol (17β-estradiol) is a white, crystalline solid, chemically described as estra-1,3,5,(10)-triene-3, 17β-diol.

Inactive Ingredients: Colloidal silicon dioxide, corn starch, dibasic calcium phosphate, lactose monohydrate, magnesium stearate, and sodium starch glycolate. In addition, the 1 mg also contains FD&C blue no. 1 aluminum lake and D&C red no. 27 aluminum lake. The 2 mg also contains FD&C blue no. 1 aluminum lake and FD&C yellow no. 5 (tartrazine) aluminum lake.

Clinical Pharmacology

Endogenous estrogens are largely responsible for the development and maintenance of the female reproductive system and secondary sexual characteristics. Although circulating estrogens exist in a dynamic equilibrium of metabolic interconversions, estradiol is the principal intracellular human estrogen and is substantially more potent than its metabolites, estrone and estriol at the receptor level.

The primary source of estrogen in normally cycling adult women is the ovarian follicle, which secretes 70 to 500 mcg of estradiol daily, depending on the phase of the menstrual cycle. After menopause, most endogenous estrogen is produced by conversion of androstenedione, secreted by the adrenal cortex, to estrone by peripheral tissues. Thus, estrone and the sulfate conjugated form, estrone sulfate, are the most abundant circulating estrogens in postmenopausal women.

Estrogens act through binding to nuclear receptors in estrogen-responsive tissues. To date, two estrogen receptors have been identified. These vary in proportion from tissue to tissue.

Circulating estrogens modulate the pituitary secretion of the gonadotropins, luteinizing hormone (LH) and follicle stimulating hormone (FSH), through a negative feedback mechanism. Estrogens act to reduce the elevated levels of these hormones seen in postmenopausal women.

Pharmacokinetics

Distribution

The distribution of exogenous estrogens is similar to that of endogenous estrogens. Estrogens are widely distributed in the body and are generally found in higher concentrations in the sex hormone target organs. Estrogens circulate in the blood largely bound to sex hormone binding globulin (SHBG) and albumin.

Metabolism

Exogenous estrogens are metabolized in the same manner as endogenous estrogens. Circulating estrogens exist in a dynamic equilibrium of metabolic interconversions. These transformations take place mainly in the liver. Estradiol is converted reversibly to estrone, and both can be converted to estriol, which is the major urinary metabolite. Estrogens also undergo enterohepatic recirculation via sulfate and glucuronide conjugation in the liver, biliary secretion of conjugates into the intestine, and hydrolysis in the gut followed by reabsorption. In postmenopausal women, a significant proportion of the circulating estrogens exist as sulfate conjugates, especially estrone sulfate, which serves as a circulating reservoir for the formation of more active estrogens.

Excretion

Estradiol, estrone, and estriol are excreted in the urine along with glucuronide and sulfate conjugates.

Special Populations

No pharmacokinetic studies were conducted in special populations, including patients with renal or hepatic impairment.

Drug Interactions

In vitro and in vivo studies have shown that estrogens are metabolized partially by cytochrome P450 3A4 (CYP3A4). Therefore, inducers or inhibitors of CYP3A4 may affect estrogen drug metabolism. Inducers of CYP3A4 such as St. John’s Wort preparations (Hypericum perforatum), phenobarbital, carbamazepine, and rifampin may reduce plasma concentrations of estrogens, possibly resulting in a decrease in therapeutic effects and/or changes in the uterine bleeding profile. Inhibitors of CYP3A4 such as erythromycin, clarithromycin, ketoconazole, itraconazole, ritonavir and grapefruit juice may increase plasma concentrations of estrogens and may result in side effects.

Clinical Studies

Osteoporosis

Most prospective studies of efficacy for this indication have been carried out in white menopausal women, without stratification by other risk factors, and tend to show a universally salutary effect on bone.

The results of a two-year, randomized, placebo-controlled, double-blind, dose-ranging study have shown that treatment with 0.5 mg estradiol daily for 23 days (of a 28 day cycle) prevents vertebral bone mass loss in postmenopausal women. When estrogen therapy is discontinued, bone mass declines at a rate comparable to the immediate postmenopausal period. There is no evidence that estrogen replacement therapy restores bone mass to premenopausal levels.

Women's Health Initiative Studies

The Women’s Health Initiative (WHI) enrolled a total of 27,000 predominantly healthy postmenopausal women to assess the risks and benefits of either the use of oral 0.625 mg conjugated estrogens (CE) per day alone or the use of oral 0.625 mg conjugated estrogens plus 2.5 mg medroxyprogesterone acetate (MPA) per day compared to placebo in the prevention of certain chronic diseases. The primary endpoint was the incidence of coronary heart disease (CHD) (nonfatal myocardial infarction and CHD death), with invasive breast cancer as the primary adverse outcome studied. A “global index” included the earliest occurrence of CHD, invasive breast cancer, stroke, pulmonary embolism (PE), endometrial cancer, colorectal cancer, hip fracture, or death due to other cause. The study did not evaluate the effects of CE or CE/MPA on menopausal symptoms.

The CE/MPA substudy was stopped early because, according to the predefined stopping rule, the increased risk of breast cancer and cardiovascular events exceeded the specified benefits included in the “global index.” Results of the CE/MPA substudy, which included 16,608 women (average age of 63 years, range 50 to 79; 83.9% White, 6.5% Black, 5.5% Hispanic), after an average follow-up of 5.2 years are presented in Table 1 below:

Table 1: RELATIVE AND ABSOLUTE RISK SEEN IN THE CE/MPA SUBSTUDY OF WHI*

*
adapted from JAMA, 2002; 288:321-333
†
a subset of the events was combined in a “global index”, defined as the earliest occurrence of CHD events, invasive breast cancer, stroke, pulmonary embolism, endometrial cancer, colorectal cancer, hip fracture, or death due to other causes
‡
nominal confidence intervals unadjusted for multiple looks and multiple comparisons
§
includes metastatic and non-metastatic breast cancer with the exception of in situ breast cancer
¶
not included in Global Index

Event †

Relative Risk
CE/MPA vs placebo
at 5.2 Years

(95% CI‡) Placebo
n = 8102

CE/MPA

n = 8506

Absolute Risk per 10,000 Women-years

CHD events
Non-fatal MI
CHD death 1.29 (1.02 to 1.63)
1.32 (1.02 to 1.72)
1.18 (0.70 to 1.97) 30
23
6 37
30
7
Invasive breast cancer§ 1.26 (1.00 to 1.59) 30 38
Stroke 1.41 (1.07 to 1.85) 21 29
Pulmonary embolism 2.13 (1.39 to 3.25) 8 16
Colorectal cancer 0.63 (0.43 to 0.92) 16 10
Endometrial cancer 0.83 (0.47 to 1.47) 6 5
Hip fracture 0.66 (0.45 to 0.98) 15 10
Death due to causes other than the events above 0.92 (0.74 to 1.14) 40 37
Global Index† 1.15 (1.03 to 1.28) 151 170
Deep vein thrombosis¶ 2.07 (1.49 to 2.87) 13 26
Vertebral fractures¶ 0.66 (0.44 to 0.98) 15 9
Other osteoporotic fractures¶ 0.77 (0.69 to 0.86) 170 131

For those outcomes included in the “global index,” the absolute excess risks per 10,000 women-years in the group treated with CE/MPA were 7 more CHD events, 8 more strokes, 8 more PEs, and 8 more invasive breast cancers, while the absolute risk reductions per 10,000 women-years were 6 fewer colorectal cancers and 5 fewer hip fractures. The absolute excess risk of events included in the “global index” was 19 per 10,000 women-years. There was no difference between the groups in terms of all-cause mortality. (See BOXED WARNINGS, WARNINGS, and PRECAUTIONS.)

Women's Health Initiative Memory Study

The Women’s Health Initiative Memory Study (WHIMS), a substudy of WHI, enrolled 4,532 predominantly healthy postmenopausal women 65 years of age and older (47% were age 65 to 69 years, 35% were 70 to 74 years, and 18% were 75 years of age and older) to evaluate the effects of CE/MPA (0.625 mg conjugated estrogens plus 2.5 mg medroxyprogesterone acetate) on the incidence of probable dementia (primary outcome) compared with placebo.

After an average follow-up of 4 years, 40 women in the estrogen/progestin group (45 per 10,000 women-years) and 21 in the placebo group (22 per 10,000 women-years) were diagnosed with probable dementia. The relative risk of probable dementia in the hormone therapy group was 2.05 (95% CI, 1.21 to 3.48) compared to placebo. Differences between groups became apparent in the first year of treatment. It is unknown whether these findings apply to younger postmenopausal women. (See BOXED WARNING and WARNINGS, Dementia.)

Indications and Usage

Estradiol Tablets USP are indicated in the:

Treatment of moderate to severe vasomotor symptoms associated with the menopause.
Treatment of moderate to severe symptoms of vulvar and vaginal atrophy associated with the menopause. When prescribing solely for the treatment of symptoms of vulvar and vaginal atrophy, topical vaginal products should be considered.
Treatment of hypoestrogenism due to hypogonadism, castration or primary ovarian failure.
Treatment of breast cancer (for palliation only) in appropriately selected women and men with metastatic disease.
Treatment of advanced androgen-dependent carcinoma of the prostate (for palliation only).
Prevention of osteoporosis. When prescribing solely for the prevention of postmenopausal osteoporosis, therapy should only be considered for women at significant risk of osteoporosis and for whom non-estrogen medications are not considered to be appropriate. (See CLINICAL PHARMACOLOGY, Clinical Studies.)

The mainstays for decreasing the risk of postmenopausal osteoporosis are weight bearing exercise, adequate calcium and vitamin D intake, and when indicated, pharmacologic therapy. Postmenopausal women require an average of 500 mg/day of elemental calcium. Therefore, when not contraindicated, calcium supplementation may be helpful for women with suboptimal dietary intake. Vitamin D supplementation of 400-800 IU/day may also be required to ensure adequate daily intake in postmenopausal women.

Contraindications

Estrogens should not be used in individuals with any of the following conditions:

Undiagnosed abnormal genital bleeding.
Known, suspected or history of cancer of the breast except in appropriately selected patients being treated for metastatic disease.
Known or suspected estrogen-dependent neoplasia.
Active deep vein thrombosis, pulmonary embolism or history of these conditions.
Active or recent (e.g., within the past year) arterial thromboembolic disease (e.g., stroke, myocardial infarction.
Liver dysfunction or disease.
Estradiol Tablets USP should not be used in patients with known hypersensitivity to its ingredients. Estradiol Tablets, USP 2 mg, contain FD&C Yellow No. 5 (tartrazine) which may cause allergic-type reactions (including bronchial asthma) in certain susceptible individuals. Although the overall incidence of FD&C Yellow No. 5 (tartrazine) sensitivity in the general population is low, it is frequently seen in patients who also have aspirin hypersensitivity.
Known or suspected pregnancy. There is no indication for estradiol tablets in pregnancy. There appears to be little or no increased risk of birth defects in children born to women who have used estrogens and progestins from oral contraceptives inadvertently during early pregnancy. (See PRECAUTIONS.)

Warnings

See BOXED WARNINGS.

1. Cardiovascular disorders.

Estrogen and estrogen/progestin therapy has been associated with an increased risk of cardiovascular events such as myocardial infarction and stroke, as well as venous thrombosis and pulmonary embolism (venous thromboembolism or VTE). Should any of these occur or be suspected estrogens should be discontinued immediately.

Risk factors for arterial vascular disease (e.g., hypertension, diabetes mellitus, tobacco use, hypercholesterolemia, and obesity) and/or venous thromboembolism (e.g., personal history or family history of VTE, obesity, and systemic lupus erythematosus) should be managed appropriately.

a. Coronary heart disease and stroke

In the Women’s Health Initiative (WHI) study, an increase in the number of myocardial infarctions and strokes has been observed in women receiving CE compared to placebo. These observations are preliminary, and the study is continuing. (See CLINICAL PHARMACOLOGY, Clinical Studies.)

In the CE/MPA substudy of WHI, an increased risk of coronary heart disease (CHD) events (defined as nonfatal myocardial infarction and CHD death) was observed in women receiving CE/MPA compared to women receiving placebo (37 vs 30 per 10,000 person years). The increase in risk was observed in year one and persisted.

In the same substudy of WHI, an increased risk of stroke was observed in women receiving CE/MPA compared to women receiving placebo (29 vs 21 per 10,000 women-years). The increase in risk was observed after the first year and persisted.

In postmenopausal women with documented heart disease (n = 2,763, average age 66.7 years) a controlled clinical trial of secondary prevention of cardiovascular disease (Heart and Estrogen/Progestin Replacement Study; HERS) treatment with CE/MPA (0.625 mg/2.5 mg per day) demonstrated no cardiovascular benefit. During an average follow-up of 4.1 years, treatment with CE/MPA did not reduce the overall rate of CHD events in postmenopausal women with established coronary heart disease. There were more CHD events in the CE/MPA-treated group than in the placebo group in year 1, but not during the subsequent years. Two thousand three hundred and twenty one women from the original HERS trial agreed to participate in an open label extension of HERS, HERS II. Average follow-up in HERS II was an additional 2.7 years, for a total of 6.8 years overall. Rates of CHD events were comparable among women in the CE/MPA group and the placebo group in HERS, HERS II, and overall.

Large doses of estrogen (5 mg conjugated estrogens per day), comparable to those used to treat cancer of the prostate and breast, have been shown in a large prospective clinical trial in men to increase the risks of nonfatal myocardial infarction, pulmonary embolism, and thrombophlebitis.

b.Venous thromboembolism (VTE)

In the Women’s Health Initiative (WHI) study, an increase in VTE has been observed in women receiving CE compared to placebo. These observations are preliminary, and the study is continuing. (See CLINICAL PHARMACOLOGY, Clinical Studies.)

In the CE/MPA substudy of WHI, a 2fold greater rate of VTE, including deep venous thrombosis and pulmonary embolism, was observed in women receiving CE/MPA compared to women receiving placebo. The rate of VTE was 34 per 10,000 womenyears in the CE/MPA group compared to 16 per 10,000 womenyears in the placebo group. The increase in VTE risk was observed during the first year and persisted.

If feasible, estrogens should be discontinued at least 4 to 6 weeks before surgery of the type associated with an increased risk of thromboembolism, or during periods of prolonged immobilization.

2. Malignant neoplasms

a. Endometrial cancer

The use of unopposed estrogens in women with intact uteri has been associated with an increased risk of endometrial cancer. The reported endometrial cancer risk among unopposed estrogen users is about 2- to 12- fold greater than in non-users, and appears dependent on duration of treatment and on estrogen dose. Most studies show no significant increased risk associated with use of estrogens for less than one year. The greatest risk appears associated with prolonged use—with increased risks of 15- to 24-fold for five to ten years or more—and this risk persists for 8 to over 15 years after estrogen therapy is discontinued.

Clinical surveillance of all women taking estrogen/progestin combinations is important (see PRECAUTIONS). Adequate diagnostic measures, including endometrial sampling when indicated, should be undertaken to rule out malignancy in all cases of undiagnosed persistent or recurring abnormal vaginal bleeding. There is no evidence that the use of natural estrogens results in a different endometrial risk profile than synthetic estrogens of equivalent estrogen dose. Adding a progestin to estrogen therapy has been shown to reduce the risk of endometrial hyperplasia, which may be a precursor to endometrial cancer.

b. Breast cancer

The use of estrogens and progestins by postmenopausal women has been reported to increase the risk of breast cancer. The most important randomized clinical trial providing information about this issue is the Women’s Health Initiative (WHI) substudy of CE/MPA (see CLINICAL PHARMACOLOGY, Clinical Studies). The results from observational studies are generally consistent with those of the WHI clinical trial and report no significant variation in the risk of breast cancer among different estrogens or progestins, doses, or routes of administration.

The CE/MPA substudy of WHI reported an increased risk of breast cancer in women who took CE/MPA for a mean follow-up of 5.6 years. Observational studies have also reported an increased risk for estrogen/progestin combination therapy, and a smaller increased risk for estrogen alone therapy, after several years of use. In the WHI trial and from observational studies, the excess risk increased with duration of use. From observational studies, the risk appeared to return to baseline in about five years after stopping treatment. In addition, observational studies suggest that the risk of breast cancer was greater, and became apparent earlier, with estrogen/progestin combination therapy as compared to estrogen alone therapy.

In the CE/MPA substudy, 26% of the women reported prior use of estrogen alone and/or estrogen/progestin combination hormone therapy. After a mean follow-up of 5.6 years during the clinical trial, the overall relative risk of invasive breast cancer was 1.24 (95% confidence interval 1.01-1.54), and the overall absolute risk was 41 vs 33 cases per 10,000 women-years, for CE/MPA compared with placebo. Among women who reported prior use of hormone therapy, the relative risk of invasive breast cancer was 1.86, and the absolute risk was 46 vs 25 cases per 10,000 women-years, for CE/MPA compared with placebo. Among women who reported no prior use of hormone therapy, the relative risk of invasive breast cancer was 1.09, and the absolute risk was 40 vs 36 cases per 10,000 women-years for CE/MPA compared with placebo. In the same substudy, invasive breast cancers were larger and diagnosed at a more advanced stage in the CE/MPA group compared with the placebo group. Metastatic disease was rare with no apparent difference between the two groups. Other prognostic factors such as histologic subtype, grade and hormone receptor status did not differ between the groups.

The use of estrogen plus progestin has been reported to result in an increase in abnormal mammograms requiring further evaluation. All women should receive yearly breast examinations by a healthcare provider and perform monthly breast self-examinations. In addition, mammography examinations should be scheduled based on patient age, risk factors, and prior mammogram results.

3. Dementia.

In the Women’s Health Initiative Memory Study (WHIMS), 4,532 generally healthy postmenopausal women 65 years of age and older were studied, of whom 35% were 70 to 74 years of age and 18% were 75 or older. After an average follow-up of 4 years, 40 women being treated with CE/MPA (1.8%, n = 2,229) and 21 women in the placebo group (0.9%, n = 2,303) received diagnoses of probable dementia. The relative risk for CE/MPA versus placebo was 2.05 (95% confidence interval 1.21 – 3.48), and was similar for women with and without histories of menopausal hormone use before WHIMS. The absolute risk of probable dementia for CE/MPA versus placebo was 45 versus 22 cases per 10,000 women-years, and the absolute excess risk for CE/MPA was 23 cases per 10,000 women-years. It is unknown whether these findings apply to younger postmenopausal women. (See CLINICAL PHARMACOLOGY, Clinical Studies and PRECAUTIONS, Geriatric Use.)

It is unknown whether these findings apply to estrogen alone therapy.